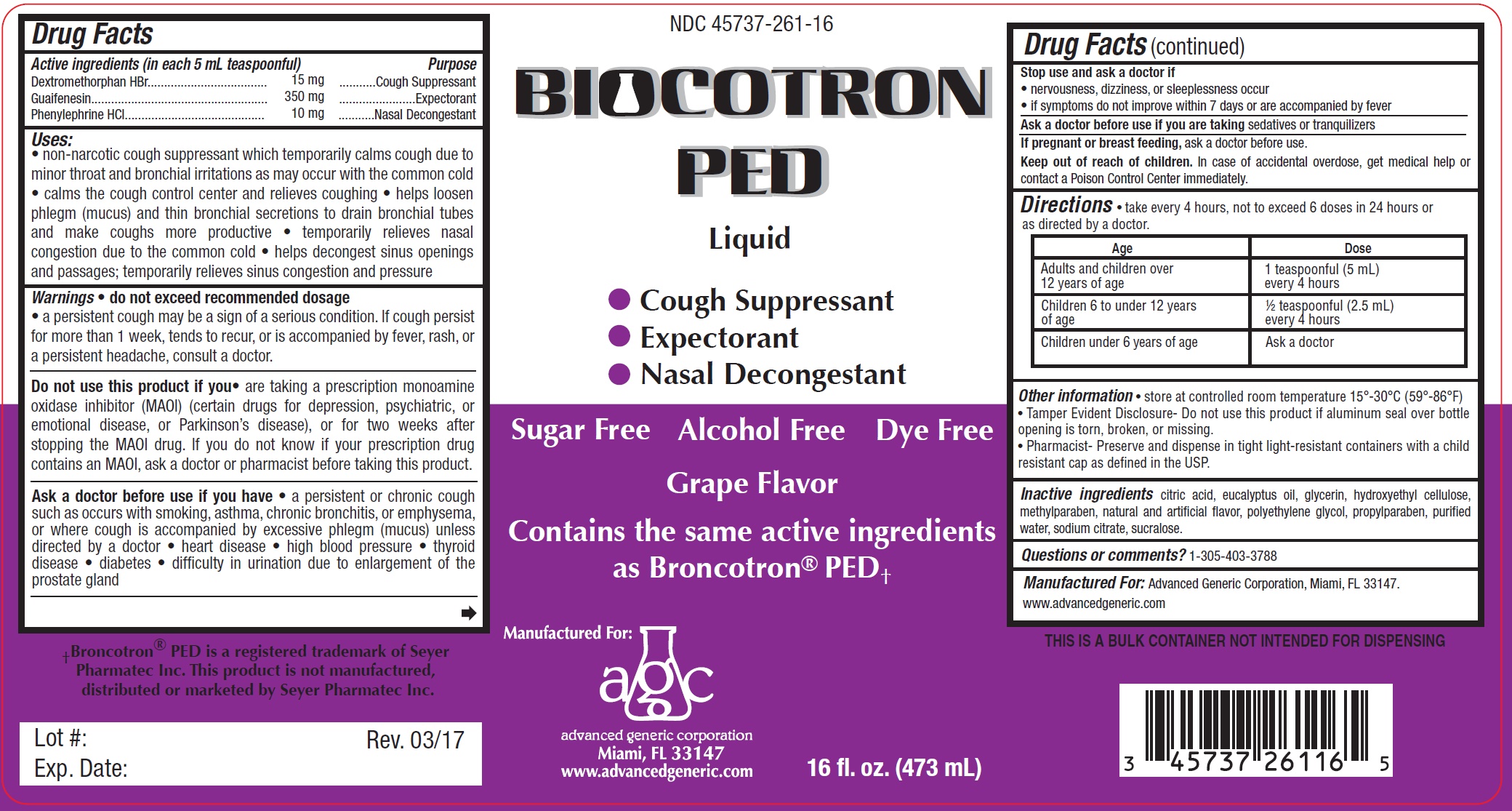 DRUG LABEL: Biocotron
NDC: 45737-261 | Form: LIQUID
Manufacturer: Advanced Generic Corporation
Category: otc | Type: HUMAN OTC DRUG LABEL
Date: 20241220

ACTIVE INGREDIENTS: DEXTROMETHORPHAN HYDROBROMIDE 15 mg/5 mL; GUAIFENESIN 350 mg/5 mL; PHENYLEPHRINE HYDROCHLORIDE 10 mg/5 mL
INACTIVE INGREDIENTS: ANHYDROUS CITRIC ACID; EUCALYPTUS OIL; GLYCERIN; HYDROXYETHYL CELLULOSE (100 MPA.S AT 2%); METHYLPARABEN; POLYETHYLENE GLYCOL, UNSPECIFIED; PROPYLPARABEN; WATER; SODIUM CITRATE; SUCRALOSE

AGC-Biocotron Ped 261

Active Ingredients (in each 5mL) Purpose

Dextromethorphan HBr, 15 mg ................................. Cough Suppressant

Guaifenesin, 350 mg ................................................ Expectorant

Phenylephrine HCl, 10 mg ...................................... Nasal Decongestant

Purpose

Cough Suppressant

Expectorant

Nasal Decongestant

Uses

- non-narcotic cough suppressant which temporarily calms cough due to minor throat and bronchial irritation as may occur with the common cold
- calms the cough control center and relieves coughing
- helps loosen phlegm (mucus) and thin bronchial secretions to drain bronchial tubes and make coughs more productive.
- temporarily relieves nasal congestion due to the common cold
- helps decongest sinus openings and passages; temporarily relieves sinus congestion and pressure

Warnings:

Do no exceed recommended dosage

a persistent cough may be a sign of a serious condition. If cough persist for more than 1 week, tends to recur, or is accompanied by fever, rash or a persistent headache, constult a doctor

Do not use this product if you

are now taking a prescription monoamine oxidase inhibitor (MAOI) (certain drugs for depression, psychiatric or emotional condition. or for two weeks after stopping the MAOI drug. If you do not know if your prescription drug contains a MAOI, ask a doctor or phamacist before taking thie product.
Ask doctor or pharmacist before use if you have

- a persistent or chronic cough such as occurs with smoking, asthma, chronic bronchitis, or emphysema, or where cough is accompanied by excessive phlegm (mucus) unless directed by a doctor.
- high blood pressure
- heart disease
- thyroid disease
- diabetes
- difficulty in urincation due to enlargment of the prostate gland

Stop use and ask a doctor if:

- nervousness, dizziness, or sleeplessness occur.
- if symptoms do not improve within 7 days or are accompanied by fever

Ask a doctor before use if you are takingsedatives or tranquilizers.

KEEP OUT OF REACH OF CHILDREN

Keep out of the reach of children.In case of accidental overdose, get medical help or contact a Poison Control Center right away.

PREGNANCY OR BREAST FEEDING

If pregnant or breast-feeding, ask a doctor before use.

DOSAGE AND ADMINISTRATION

Directions:Take very 4 hours, not to exceed 6 doses in 24 hours or as directed by physician

Age | Dose
Adults and children 12 years of age or older | 1 teaspoonful (5 mL) every 4 hours
Children 6 to under 12 years of age | 1/2 teaspoonful (2.5 mL) every 4 hours
Children under 6 years of age | Ask a doctor

INACTIVE INGREDIENT

Inactive ingredients: citric acid, eucalyptus oil, glycerin, hydroxyethyl cellulose, methylparaben, natural and artificial flavor, polyethylene glycol, propylparaben, purified water, sodium citrate, sucralose.

Questions or comments?1-305-403-3788